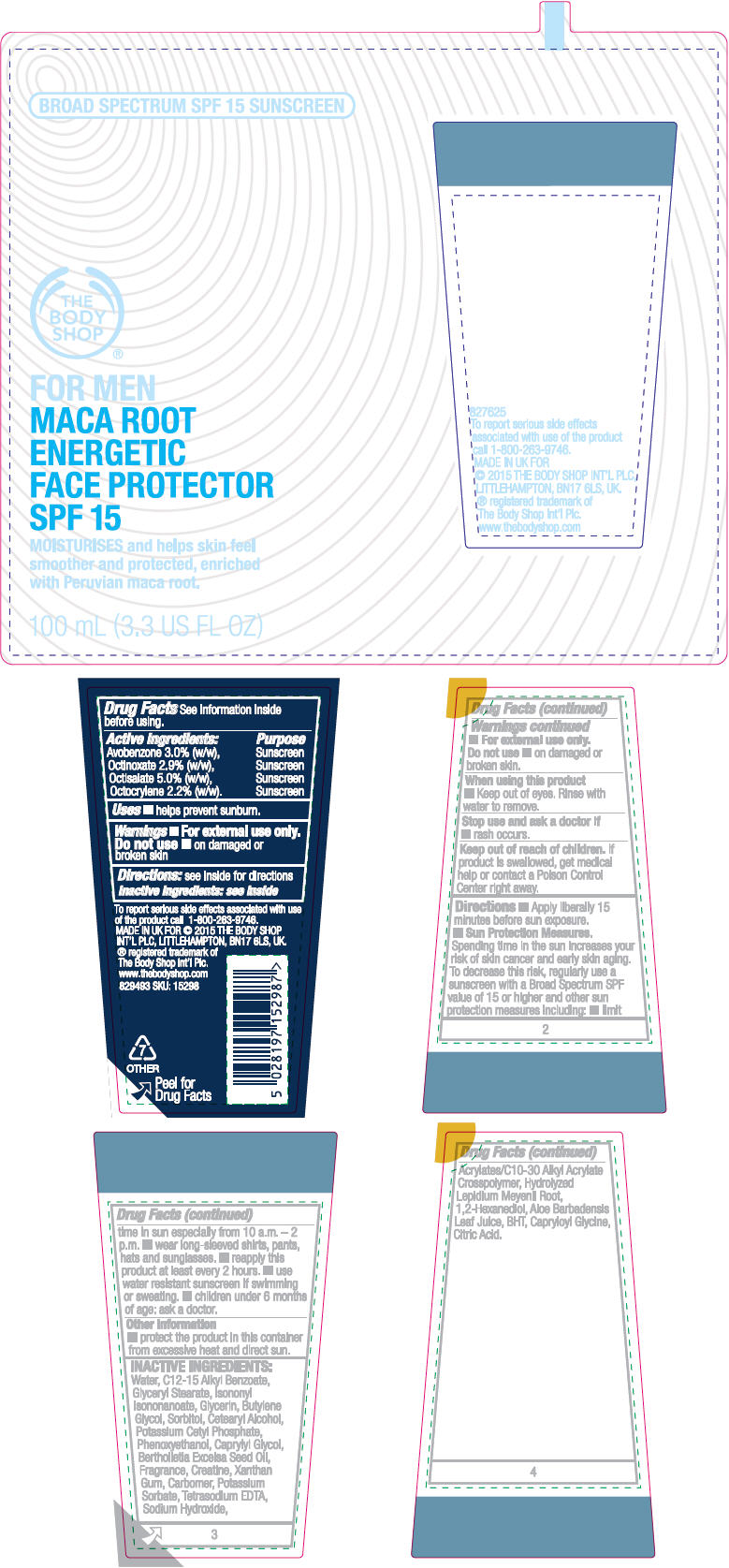 DRUG LABEL: For Men Maca Root Energetic Face Protector SPF 15
NDC: 57691-298 | Form: LOTION
Manufacturer: Buth-Na-Bodhaige, Inc.,
Category: otc | Type: HUMAN OTC DRUG LABEL
Date: 20161010

ACTIVE INGREDIENTS: Octisalate 0.05 g/1 mL; Avobenzone 0.03 g/1 mL; Octinoxate 0.029 g/1 mL; Octocrylene 0.022 g/1 mL
INACTIVE INGREDIENTS: Water; Alkyl (C12-15) Benzoate; GLYCERYL MONOSTEARATE; Isononyl Isononanoate; Glycerin; Butylene Glycol; Sorbitol; Cetostearyl Alcohol; Potassium Cetyl Phosphate; Phenoxyethanol; Caprylyl Glycol; Brazil Nut Oil; Creatine; Xanthan Gum; Potassium Sorbate; EDETATE SODIUM; Sodium Hydroxide; CARBOMER INTERPOLYMER TYPE A (ALLYL SUCROSE CROSSLINKED); HYDROLYSED LEPIDIUM MEYENII ROOT (ENZYMATIC); 1,2-Hexanediol; ALOE VERA LEAF; BUTYLATED HYDROXYTOLUENE; Capryloyl Glycine; CITRIC ACID MONOHYDRATE

For Men Maca Root Energetic Face Protector SPF 15

Drug Facts

ACTIVE INGREDIENT

Active Ingredients: | Purpose
Avobenzone 3.0% (w/w), | Sunscreen
Octinoxate 2.9% (w/w), | Sunscreen
Octisalate 5.0% (w/w), | Sunscreen
Octocrylene 2.2% (w/w). | Sunscreen

Uses

- helps prevent sunburn.

Warnings

- For external use only.

Do not use

- on damaged or broken skin.

When using this product

- Keep out of eyes. Rinse with water to remove.

Stop use and ask a doctor if

- rash occurs.

Keep out of reach of children. If product is swallowed, get medical help or contact a Poison Control Center right away.

Directions

- Apply liberally 15 minutes before sun exposure.
- Sun Protection Measures. Spending time in the sun increases your risk of skin cancer and early skin aging. To decrease this risk, regularly use a sunscreen with a Broad Spectrum SPF value of 15 or higher and other sun protection measures including:
  - limit time in sun especially from 10 a.m. – 2 p.m.
  - wear long-sleeved shirts, pants, hats and sunglasses.
- reapply this product at least every 2 hours.
- use water resistant sunscreen if swimming or sweating.
- children under 6 months of age: ask a doctor.

Other information

- protect the product in this container from excessive heat and direct sun.

INACTIVE INGREDIENTS

Water, C12-15 Alkyl Benzoate, Glyceryl Stearate, Isononyl Isononanoate, Glycerin, Butylene Glycol, Sorbitol, Cetearyl Alcohol, Potassium Cetyl Phosphate, Phenoxyethanol, Caprylyl Glycol, Bertholletia Excelsa Seed Oil, Fragrance, Creatine, Xanthan Gum, Carbomer, Potassium Sorbate, Tetrasodium EDTA, Sodium Hydroxide, Acrylates/C10-30 Alkyl Acrylate Crosspolymer, Hydrolyzed Lepidium Meyenii Root, 1,2-Hexanediol, Aloe Barbadensis Leaf Juice, BHT, Capryloyl Glycine, Citric Acid.

QUESTIONS

To report serious side effects associated with use of the product call 1-800-263-9746.

PRINCIPAL DISPLAY PANEL - 100 mL Tube Label

BROAD SPECTRUM SPF 15 SUNSCREEN

THE
BODY
SHOP®

FOR MEN
MACA ROOT
ENERGETIC
FACE PROTECTOR
SPF 15

MOISTURISES and helps skin feel
smoother and protected, enriched
with Peruvian maca root.

100 mL (3.3 US FL OZ)